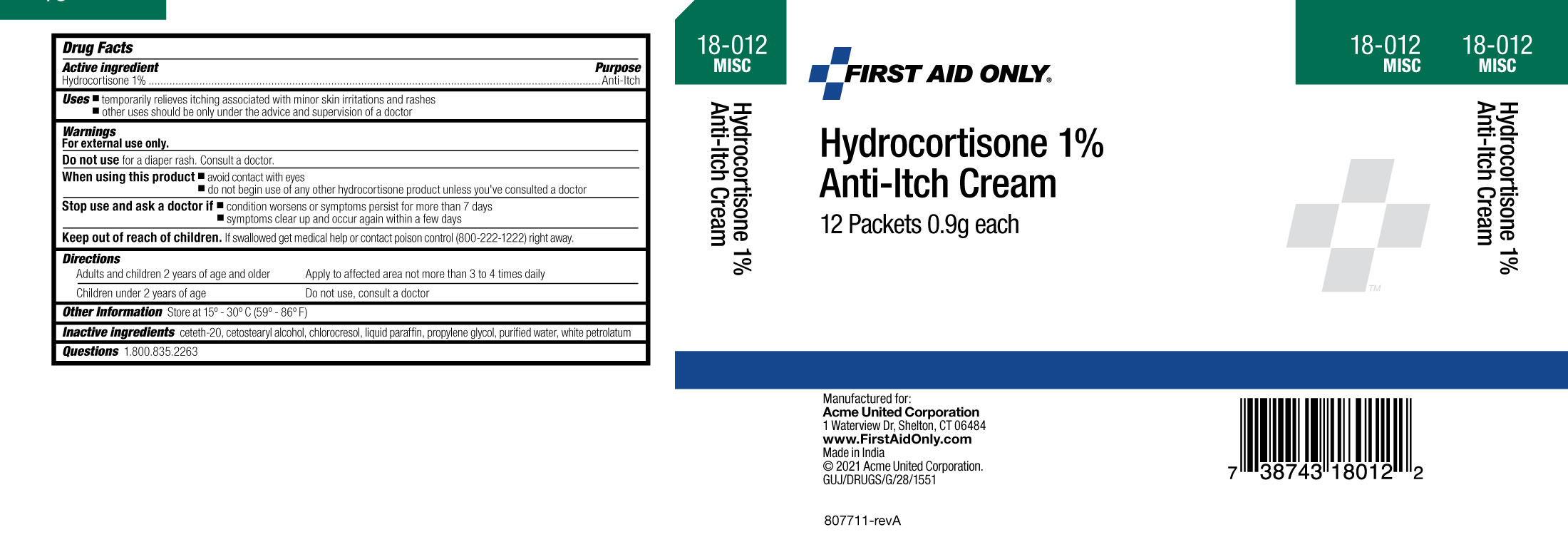 DRUG LABEL: First Aid Only Hydrocortisone 1% Anti-Itch
NDC: 0924-5633 | Form: CREAM
Manufacturer: Acme United Corporation
Category: otc | Type: HUMAN OTC DRUG LABEL
Date: 20241119

ACTIVE INGREDIENTS: HYDROCORTISONE 10 mg/1 g
INACTIVE INGREDIENTS: CETETH-20; CETOSTEARYL ALCOHOL; MINERAL OIL; CHLOROCRESOL; PROPYLENE GLYCOL; WATER; PETROLATUM

First Aid Only Hydocortisone 1% Anti-Itch Cream

ACTIVE INGREDIENT

Hydrocortisone 1%

PURPOSE

Anti-Itch

USES

Uses ▪ temporarily relieves itching associated with minor skin irritations and rashes

▪other uses should be only under the advice and supervision of a doctor

WARNINGS

For external use only.

Do not use

for a diaper rash. Consult a doctor.

When using this product

- Avoid contact with the eyes
- Do not begin use of any other Hydrocortisone product unless you have asked a doctor

Stop use and ask a doctor if

▪ condition worsens or symptoms persist for more than 7 days

▪ symptoms clear up and occur again within a few days

Keep out of reach of children.If swallowed get medical help or contact poison control (800-222-1222) right away.

DIRECTIONS

Adults and children 2 years of age and older Apply to affected area not more than 3 to 4 times daily

Children under 2 years of age Do not use, consult a doctor

OTHER INFORMATION

- Store at 15° to 30°C (59° to 86°F)

INACTIVE INGREDIENTS

ceteth-20, cetostearyl alcohol, chlorocresol, liquid paraffin, propylene glycol, purified water, soft paraffin

Questions 1.800.835.2263

PACKAGE LABEL

Carton image